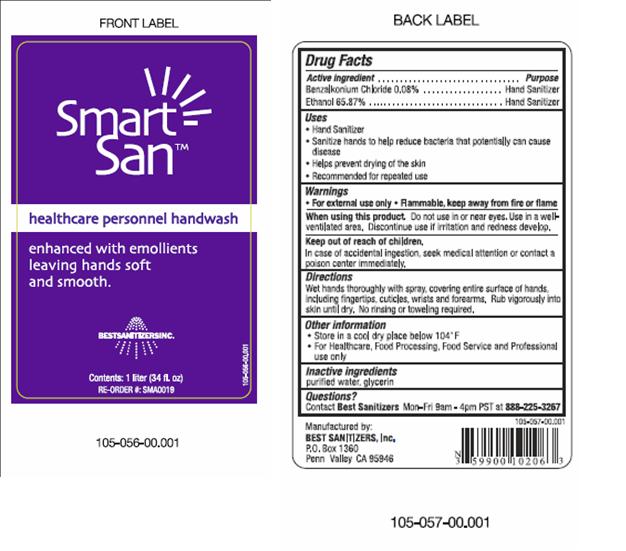 DRUG LABEL: Smart San Healthcare Personnel Handwash
NDC: 59900-102 | Form: LIQUID
Manufacturer: Best Sanitizers, Inc
Category: otc | Type: HUMAN OTC DRUG LABEL
Date: 20190103

ACTIVE INGREDIENTS: ALCOHOL 65.87 mL/100 mL; BENZALKONIUM CHLORIDE 0.08 g/100 mL
INACTIVE INGREDIENTS: WATER; GLYCERIN

Smart San Healthcare Personnel Handwash

Active Ingredient

Benzalkonium Chloride 0.8%

Ethanol 65.87%

Purpose

Hand Sanitizer

Uses

- Hand Sanitizer
- Sanitize hands to help reduce bacteria hat potentially can cause disease
- Helps prevent drying of the skin
- Recommended for repeated use

Warnings

- For external use only
- Flammable, keep away from fire or flame

When Using this product

Do not use in or near eyes.

Use in a well ventilated area.

Discontinue use if irritation and redness develop.

Keep out of reach of children

In case of accidental ingestion seek medical attention or contact a poison center immediately.

Directions

Wet hands thoroughly with spray, covering entire surface of hands, including fingertips cuticles wrists and forearms, Rub vigorously into skin until dry. No rinsing or toweling required.

Other Information

- Store in a cool dry place below 104° F
- For Healthcare, Food Processing, Food Services and Professional use only

Inactive ingredients

purified water, glycerin

Questions?

Contact Best Sanitizers Mon-Fri 9am - 4pm PST at 888-225-3267

PACKAGE LABEL

NDC 59900-111-05

NDC 59900-111-06

Smart San™
Healthcare Personnel Handwash